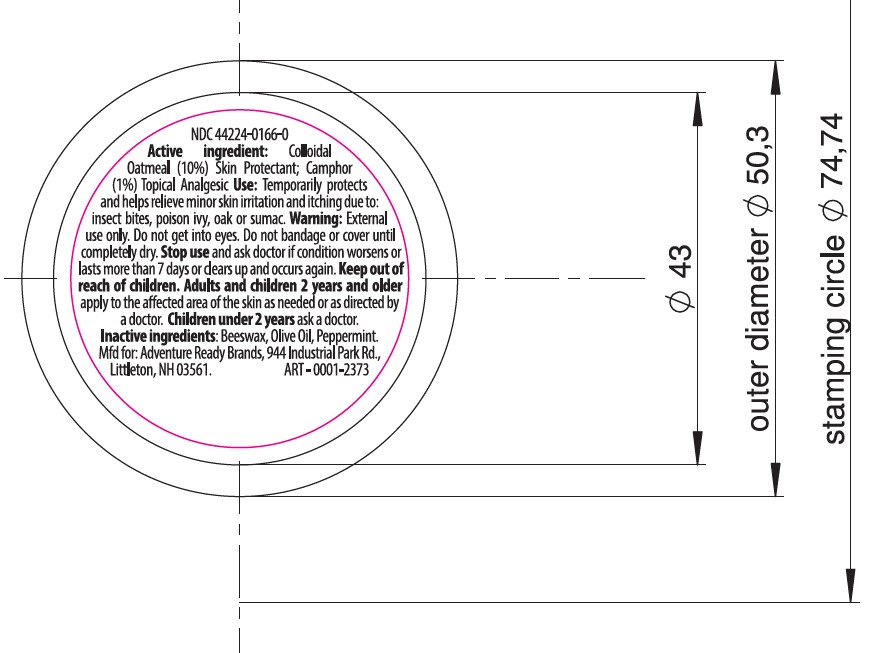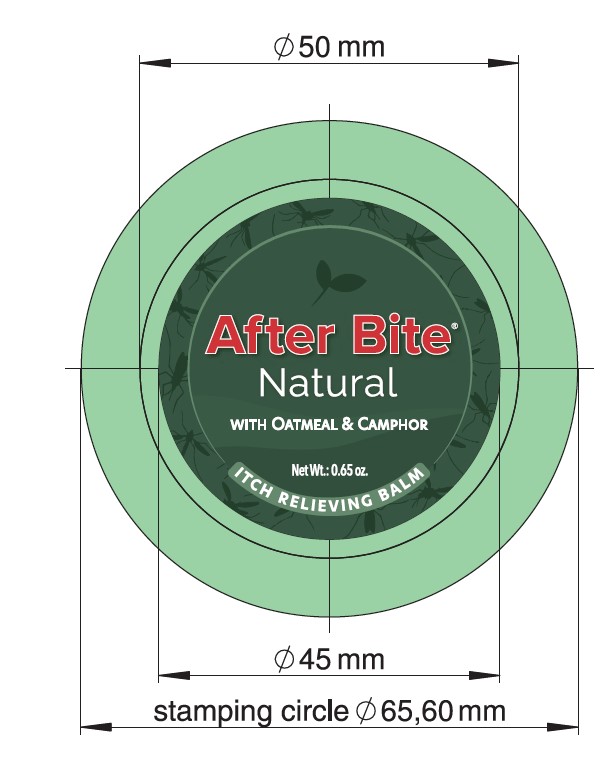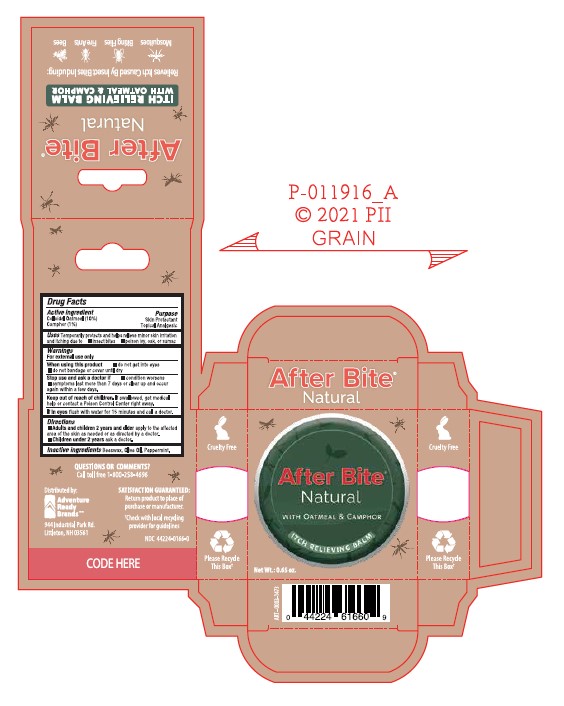 DRUG LABEL: After Bite Natural
NDC: 44224-0166 | Form: SALVE
Manufacturer: Adventure Ready Brands
Category: otc | Type: HUMAN OTC DRUG LABEL
Date: 20230119

ACTIVE INGREDIENTS: OATMEAL 100 mg/1 g; CAMPHOR (NATURAL) 10 mg/1 g
INACTIVE INGREDIENTS: PEG-8 BEESWAX; OLIVE OIL; PEPPERMINT OIL

After Bite Natural

Drug Facts

Active Ingredient

Collodial Oatmeal (10%)

Camphor (1%)

Purpose

Skin Protectant

Topical Analgesic

Uses

Temporarily protects and helps relieve minor skin irritation and itching due to

- insect bites
- poison ivy, oak, or sumac

Warnings

For external use only

When using this product

- do not get into eyes
- do not bandage or cover until dry

Stop use and ask doctor if

- condition worsens
- symptoms last more than 7 days or clear up and occur again within a few days

Keep out of reach of children.

If swallowed, get medical help or contact a Poison Control Center right away.

If in eyes

flush with water for 15 minutes and call a doctor.

Directions

- Adults and children 2 years and older apply to the affected area of the skin as needed or as directed by a doctor.
- Children under 2 years ask a doctor.

Inactive Ingredients

Beeswax, Olive Oil, Peppermint.